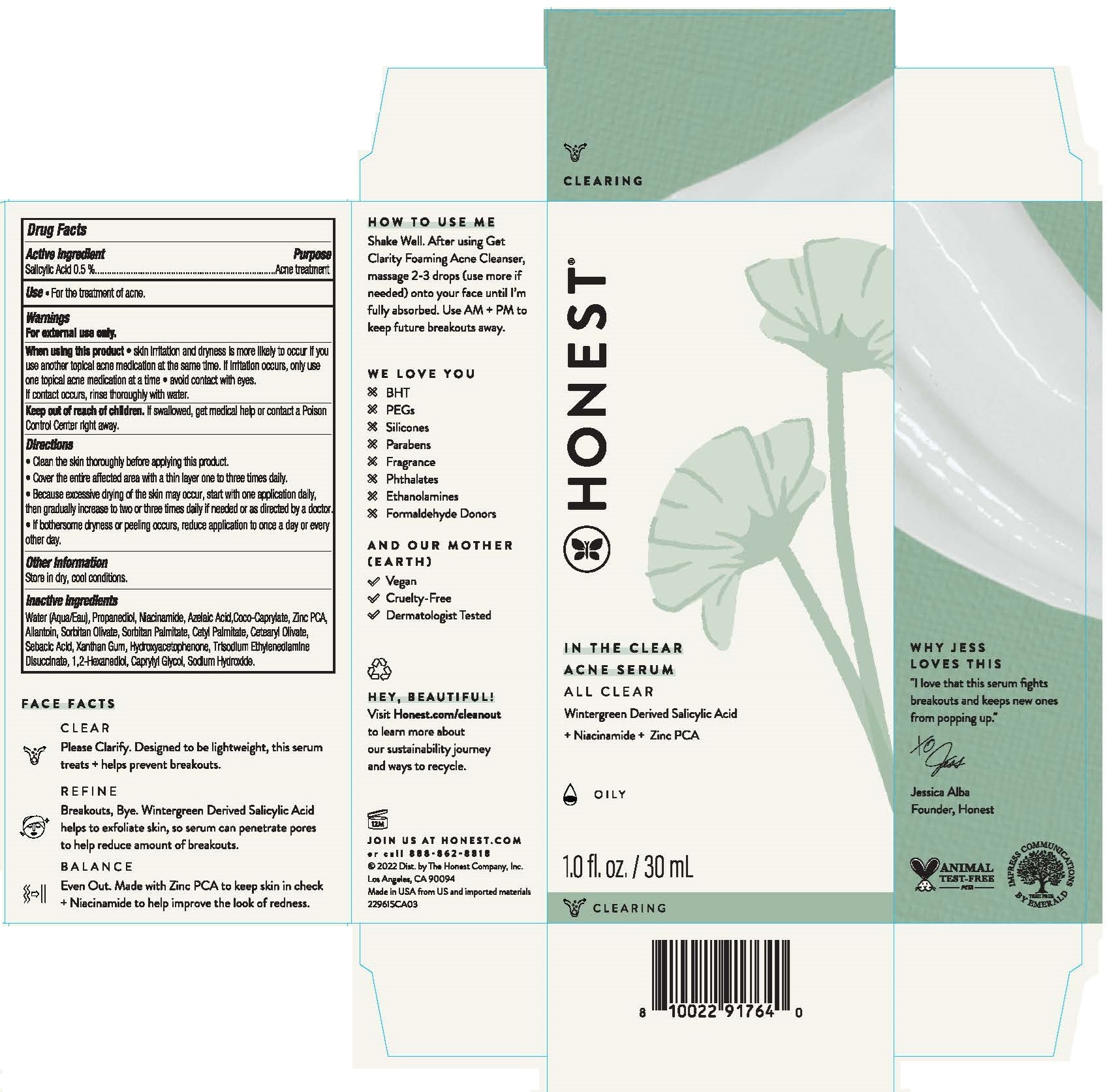 DRUG LABEL: In the Clear Acne Serum
NDC: 69366-414 | Form: LIQUID
Manufacturer: The Honest Company, Inc
Category: otc | Type: HUMAN OTC DRUG LABEL
Date: 20231219

ACTIVE INGREDIENTS: SALICYLIC ACID 0.5 g/100 mL
INACTIVE INGREDIENTS: NIACINAMIDE; COCO-CAPRYLATE; CETEARYL OLIVATE; AZELAIC ACID; ZINC PIDOLATE; ALLANTOIN; 1,2-HEXANEDIOL; WATER; TRISODIUM ETHYLENEDIAMINE DISUCCINATE; PROPANEDIOL; SORBITAN OLIVATE; SORBITAN MONOPALMITATE; CETYL PALMITATE; SEBACIC ACID; XANTHAN GUM; HYDROXYACETOPHENONE; CAPRYLYL GLYCOL; SODIUM HYDROXIDE

In the Clear Acne Serum

Active ingredient

Salicylic Acid 0.5%

Purpose

Acne treatment

INDICATIONS AND USAGE

Use• For the treatment of acne.

Warnings

For external use only.

When using this product• skin irritation and dryness is more likely to occur if you use another topical acne medication at the same time. If irritation occurs, only use one topical acne medication at a time • avoid contact with eyes. If contact occurs, rinse thoroughly with water.

Keep out of reach of children. If swallowed, get medical help or contact a Poison Control Center right away.

Directions

• Clean the skin thoroughly before applying this product.

• Cover the entire affected area with a thin layer one to three times daily.

• Because excessive drying of the skin may occur, start with one applicaiton daily, then gradually increase to two or three times daily if needed or as direted by a doctor.

• If bothersome dryness or peeling occurs, reduce application to once a day or every other day.

Other information

Store in dry, cool conditions.

Inactive ingredients

Water (Aqua/Eau), Propanediol, Niacinamide, Azelaic Acid, Coco-Caprylate, Zinc PCA, Allantoin, Sorbitan Olivate, Sorbitan Palmitate, Cetyl Palmitate, Cetearyl Olivate, Sebacic Acid, Xanthan Gum, Hydroxyacetophernone, Trisodium Ethylenedlamine Disuccinate, 1,2-Hexanediol, Caprylyl Glycol, Sodium Hydroxide.

HOW TO USE ME

Shake Well. After using Get Clarity Foaming Acne Cleanser, massage 2-3 drops (use more if needed) onto your face until I'm fully absorbed. Use AM+ PM to keep future breakouts away.

PACKAGE LABEL

HONEST®

IN THE CLEAR ACNE SERUM

ALL CLEAR

Wintergreen Derived Salicylic Acid

+ Niacinamide + Zinc PCA

1.0 fl. oz. / 30 mL

888-862-8818

©2022 Dist. by The Honest Company, Inc.

Los Angeles, CA 90094

Made in USA from US and imported materials